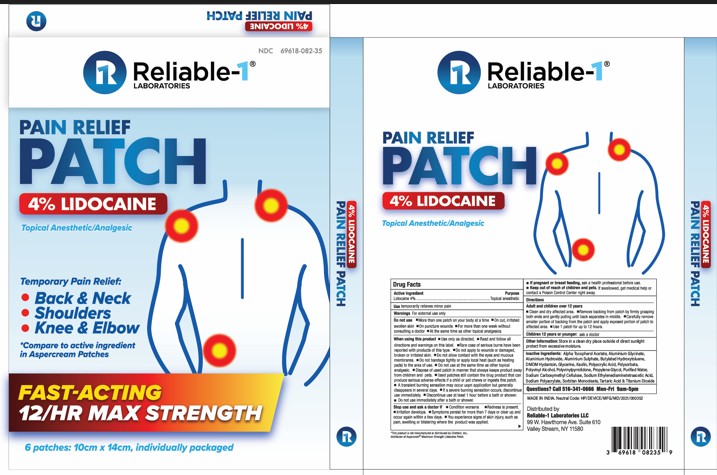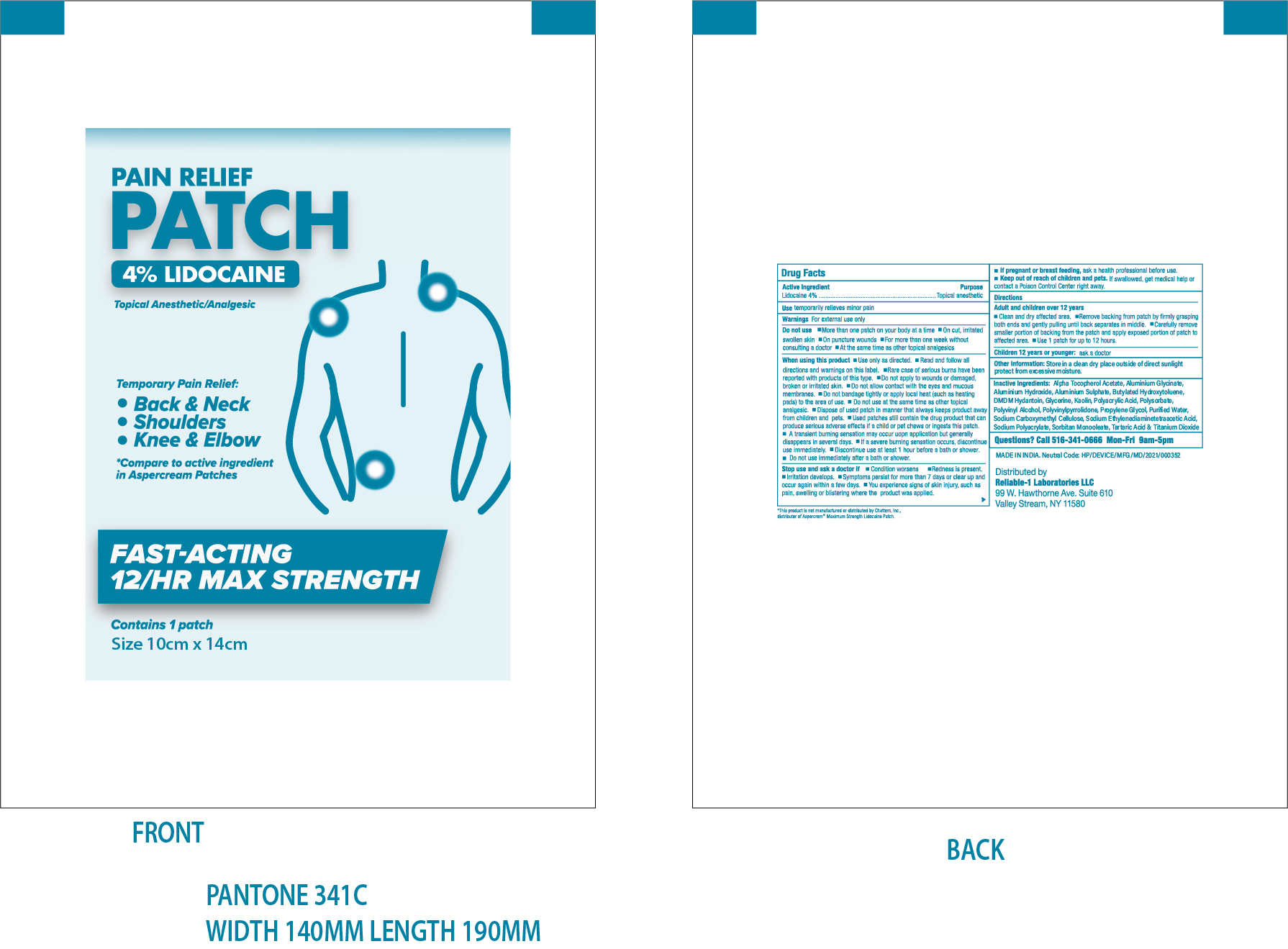 DRUG LABEL: Pain Relief Patch 4% Lidocaine
NDC: 69618-082 | Form: PATCH
Manufacturer: Reliable 1 Laboratories LLC
Category: otc | Type: HUMAN OTC DRUG LABEL
Date: 20250115

ACTIVE INGREDIENTS: LIDOCAINE 224 mg/1 1
INACTIVE INGREDIENTS: DIHYDROXYALUMINUM AMINOACETATE; ALUMINUM SULFATE; DMDM HYDANTOIN; GLYCERIN; WATER; POLAWAX POLYSORBATE; POVIDONE K30; SORBITAN MONOOLEATE; TARTARIC ACID; BUTYLATED HYDROXYTOLUENE; SODIUM POLYACRYLATE (8000 MW); PROPYLENE GLYCOL; TITANIUM DIOXIDE; .ALPHA.-TOCOPHEROL ACETATE; CARBOXYMETHYLCELLULOSE SODIUM; KAOLIN; POLYVINYL ALCOHOL; ALUMINUM HYDROXIDE

Pain Relief Patch 4% Lidocaine

ACTIVE INGREDIENT

Lidocaine 4%

PURPOSE

Topical Anesthetic

USE

Use Temporarily Relieves Minor Pain

WARNINGS

For external use only

DO NOT USE

- More than one patch on your body at a time
- On cut, irritated swollen skin
- On puncture wounds
- For more than one week without consulting a doctor
- At the same time as other topical analgesics

When using this product

- Use only as directed.
- Read and follow all directions and warnings on this label.
- Rare case of serious burns have been reported with products of this type.
- Do not apply to wounds or damaged, broken or irritated skin.
- Do not allow contact with the eyes and mucous membranes.
- Do not bandage tightly or apply local heat (such as heating pads) to the area of use.
- Do not use at the same time as other topical analgesic.
- Dispose of used patch in manner that always keeps product away from children and pets.
- Used patches still contain the drug product that can produce serious adverse effects if a child or pet chews or ingests this patch
- A transient burning sensation may occur upon application but generally disappears in several days.
- If a severe burning sensation occurs, discontinue use immediately.
- Discontinue use at least 1 hour before a bath or shower.
- Do not use immediately after a bath or shower.

Stop Use and ask doctor if

- Condition worsens
- Redness is present.
- Irritation develops.
- Symptoms persist for more than 7 days or clear up and occur again within a few days.
- You experience signs of skin injury, such as pain, swelling or blistering where the product was applied.

PREGNANCY OR BREAST FEEDING

If pregnant or breast feeding, ask a health professional before use.

Keep out of reach of children and pets. If swallowed, get medical help or contact a Poison Control Center right away.

Directions

Adult and children over 12 years

- Clean and dry affected area.
- Remove backing from patch by firmly grasping both ends and gently pulling until back separates in middle.
- Carefully remove smaller portion of backing from the patch and apply exposed portion of patch to affected area.
- Use 1 patch for up to 12 hours.

Children 12 years or younger:

- ask a doctor

Other information:

Store in a clean dry place outside of direct sunlight protect from excessive moisture.

INACTIVE INGREDIENT

Alpha Tocopherol Acetate, Aluminium Glycinate, Aluminium Hydroxide, Aluminium Sulphate, Butylated Hydroxytoluene, DMDM Hydantoin, Glycerine, Kaolin, Polyacrylic Acid, Polysorbate, Polyvinyl Alcohol, Polyvinylpyrrolidone, Propylene Glycol, Purified Water, Sodium Carboxymethyl Cellulose, Sodium Ethylenediaminetetraacetic Acid, Sodium Polyacrylate, Sorbitan Monooleate, Tartaric Acid & Titanium Dioxide.

PACKAGE LABEL

NDC 69618-082-35

Pain Relief Patch

4% Lidocaine

Topical Anesthetic/ Analgesic

Temporary Pain Relief

Back & Neck

Shoulders

Knee & Elbow

*compare to active ingredient in Aspercream Patches

Fast Acting 12/HR Max Strength

6 patches: 10cm X 14CM, individually packaged

Questions? Call 516-341-0666 Mon-Fri 9am-5pm

Distributed by

Reliable 1 Laboratories LLC

99 W. Hawthorne Ave, Suite 610

Valley Stream, NY 11580